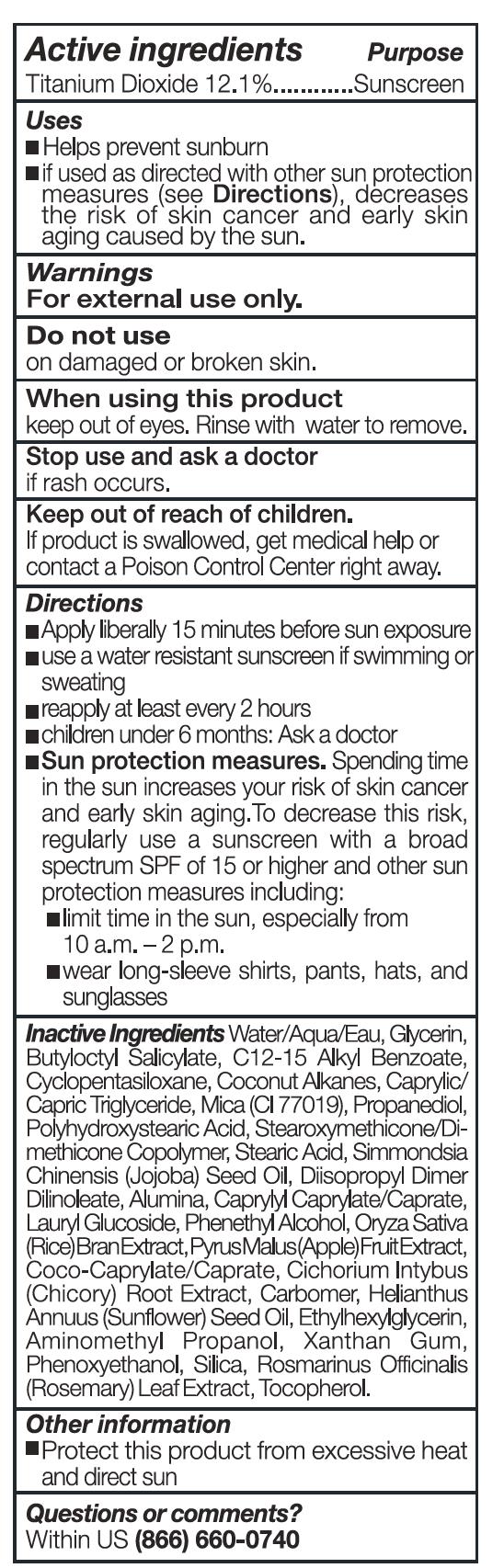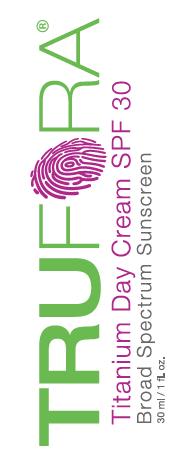 DRUG LABEL: BROAD SPECTRUM SUNSCREEN SPF 30
NDC: 69146-301 | Form: CREAM
Manufacturer: TRUTH AESTHETICS LLC
Category: otc | Type: HUMAN OTC DRUG LABEL
Date: 20180208

ACTIVE INGREDIENTS: TITANIUM DIOXIDE 12.1 mg/100 mL
INACTIVE INGREDIENTS: WATER; GLYCERIN; BUTYLOCTYL SALICYLATE; ALKYL (C12-15) BENZOATE; CYCLOMETHICONE 5; COCONUT ALKANES; MEDIUM-CHAIN TRIGLYCERIDES; MICA; PROPANEDIOL; POLYHYDROXYSTEARIC ACID (2300 MW); STEARIC ACID; JOJOBA OIL; DIISOPROPYL DILINOLEATE; ALUMINUM OXIDE; CAPRYLYL CAPRYLATE/CAPRATE; LAURYL GLUCOSIDE; PHENYLETHYL ALCOHOL; RICE BRAN; APPLE; FERRIC OXIDE RED; COCO-CAPRYLATE/CAPRATE; CHICORY ROOT; CARBOXYMETHYLCELLULOSE SODIUM; SUNFLOWER OIL; ETHYLHEXYLGLYCERIN; AMINOMETHYLPROPANOL; XANTHAN GUM; PHENOXYETHANOL; SILICON DIOXIDE; ROSEMARY; TOCOPHEROL

TITANIUM DAY CREAM SPF 30

Back Panel - Active Ingredient

Titanium Dioxide 12.1%

Back Panel - Purpose

Sunscreen

Back Panel - Uses

- Helps prevent sunburn.
- if used as directed with other sun protection measures (see Directions), decreases the risk of skin cancer and early skin aging caused by the sun.

Back Panel - Directions

Directions

- Apply liberally 15 minutes before sun exposure
- use a water resistant sunscreen if swimming or sweating
- reapply at least every 2 hours
- children under 6 months: Ask a doctor
- Sun protection measures. Spending time in the sun increases your risk of skin cancer and early skin aging. To decrease this risk, regularly use a sunscreen with a board spectrum SPF of 15 or higher and other sun protection measures including
  - limit time in the sun, especially from 10 a.m. - 2 p.m.
  - wear long-sleeve shirts, pants, hats, and sunglasses

Back Panel - Warnings

Warnings

For external use only.

----------------------------------------------------------

Do not use

on damaged or broken skin

----------------------------------------------------------

When using this product

keep out of eyes. Rinse with water to remove.

-----------------------------------------------------------

Stop use and ask doctor

if rash occurs

----------------------------------------------------------

Keep out of reach of children.

If product is swallowed, get medical help or

contact a Poison Control Center right away.

Back Panel - Inactive Ingredients

Inactive Ingredients: Water/Aqua/EAU, Glycerin, Butyloctyl Salicylate, C12-15 Alkyl Benzoate, Cyclopentasiloxane, coconut Alkanes, Caprylic / Capric Triglycerine, Mica (CI77019), Propanediol, Polyhydroxystearic Acid, Stearoxymethicone / Dimenthicone Copolymer, Stearic Acid, Simmondsia Chinensis (Jojoba) Seed Oil, Diisopropyl Dimer Dilinoleate, Alumina, Caprylyl Caprylate / Caprate, Lauryl Glucoside, Phenethyl Alcohol, Oriza Sativa (Rice) Bran Extract, Pyrus Malus (Apple) Fruit Extract, Coco- Caprylate / Caprate, Cichorium Intybus (Chicory) Root Extract, Carbomer, Helianthus Annuus (Sunflower) Seed Oil, Ethylhexylglycerin, Aminomethyl Propanol, Xanthan Gum, Phenoxyethanol, Silica, Rosmarinus Officinalis (Rosemary) Leaf Extract, Tocopherol.

Questions or comments?

Within US (866) 660-0740

Front Panel - PDP

TRUFORA

Titanium Day Cream SPF 30

Broad Spectrum Sunscreen

30 ml / 1 fl. oz